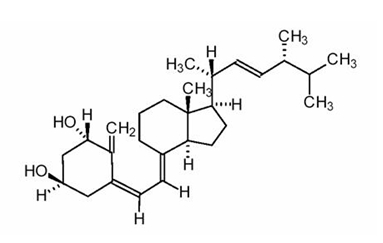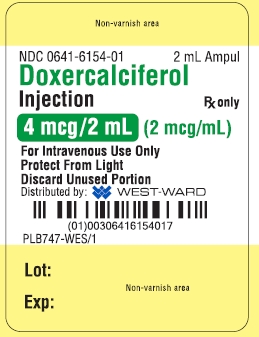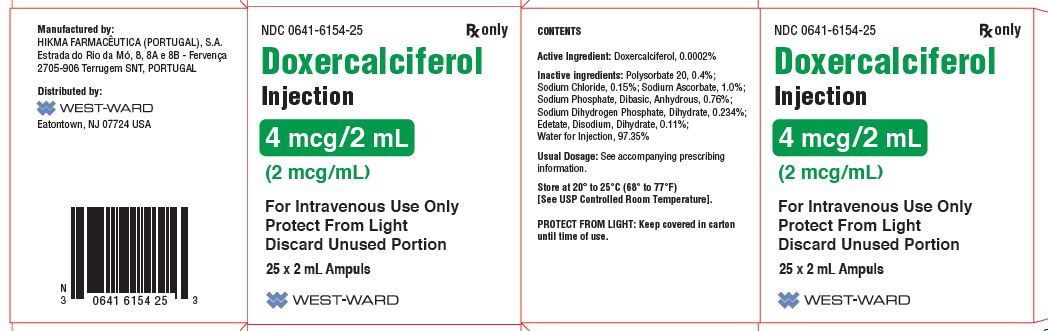 DRUG LABEL: Doxercalciferol
NDC: 0641-6154 | Form: INJECTION
Manufacturer: Hikma Pharmaceuticals USA Inc.
Category: prescription | Type: HUMAN PRESCRIPTION DRUG LABEL
Date: 20191230

ACTIVE INGREDIENTS: DOXERCALCIFEROL 2 ug/1 mL
INACTIVE INGREDIENTS: POLYSORBATE 20 4 mg/1 mL; SODIUM CHLORIDE 1.5 mg/1 mL; SODIUM ASCORBATE 10 mg/1 mL; SODIUM PHOSPHATE, DIBASIC, ANHYDROUS 7.6 mg/1 mL; SODIUM PHOSPHATE, MONOBASIC 2.3 mg/1 mL; EDETATE DISODIUM 1.1 mg/1 mL; WATER

DOXERCALCIFEROL INJECTION

Rx only

DESCRIPTION

Doxercalciferol, the active ingredient in Doxercalciferol Injection, is a synthetic vitamin D2 analog that undergoes metabolic activation in vivo to form 1a,25-dihydroxyvitamin D2 (1a,25-(OH)2D2), a naturally occurring, biologically active form of vitamin D2. Doxercalciferol injection is available as a sterile, clear, colorless aqueous solution for intravenous injection.

Doxercalciferol single-use injection is supplied in a 2 mL amber glass ampul containing 4 mcg/2 mL or 2 mcg/mL. Each milliliter (mL) of solution contains doxercalciferol, 2 mcg; Polysorbate 20, 4 mg; sodium chloride, 1.5 mg; sodium ascorbate, 10 mg; sodium phosphate, dibasic, anhydrous 7.6 mg; sodium dihydrogen phosphate, dihydrate, 2.34 mg; and disodium edetate, 1.1 mg.

Doxercalciferol is a colorless crystalline compound with a calculated molecular weight of 412.66 and a molecular formula of C28H44O2. It is soluble in oils and organic solvents, but is relatively insoluble in water. Chemically, doxercalciferol is (1α,3β,5Z,7E,22E)-9,10-secoergosta-5,7,10(19),22-tetraene-1,3-diol and has the structural formula presented in Figure 1.

Figure 1: Chemical Structure of Doxercalciferol

Other names frequently used for doxercalciferol are 1α-hydroxyvitamin D2, 1α-OH-D2, and 1α-hydroxyergocalciferol.

CLINICAL PHARMACOLOGY

Vitamin D levels in humans depend on two sources: (1) exposure to the ultraviolet rays of the sun for conversion of 7-dehydrocholesterol in the skin to vitamin D3 (cholecalciferol) and (2) dietary intake of either vitamin D2 (ergocalciferol) or vitamin D3. Vitamin D2 and vitamin D3 must be metabolically activated in the liver and kidney before becoming fully active on target tissues. The initial step in the activation process is the introduction of a hydroxyl group in the side chain at C-25 by the hepatic enzyme, CYP 27 (a vitamin D-25-hydroxylase). The products of this reaction are 25-(OH)D2 and 25-(OH)D3, respectively. Further hydroxylation of these metabolites occurs in the mitochondria of kidney tissue, catalyzed by renal 25-hydroxyvitamin D-1-α-hydroxylase to produce 1α,25-(OH)2D2, the primary biologically active form of vitamin D2, and 1α,25-(OH)2D3 (calcitriol), the biologically active form of vitamin D3.

Mechanism of Action

Calcitriol (1α,25-(OH)2D3) and 1α,25-(OH)2D2 regulate blood calcium at levels required for essential body functions. Specifically, the biologically active vitamin D metabolites control the intestinal absorption of dietary calcium, the tubular reabsorption of calcium by the kidney and, in conjunction with parathyroid hormone (PTH), the mobilization of calcium from the skeleton. They act directly on bone cells (osteoblasts) to stimulate skeletal growth, and on the parathyroid glands to suppress PTH synthesis and secretion. These functions are mediated by the interaction of these biologically active metabolites with specific receptor proteins in the various target tissues. In uremic patients, deficient production of biologically active vitamin D metabolites (due to lack of or insufficient 25-hydroxyvitamin D-1-alpha-hydroxylase activity) leads to secondary hyperparathyroidism, which contributes to the development of metabolic bone disease in patients with renal failure.

Pharmacokinetics and Metabolism

After intravenous administration, doxercalciferol is activated by CYP 27 in the liver to form 1α,25-(OH)2D2 (major metabolite) and 1α,24-dihydroxyvitamin D2 (minor metabolite). Activation of doxercalciferol does not require the involvement of the kidneys.

Peak blood levels of 1α,25-(OH)2D2 are reached at 8 +/- 5.9 hours (mean +/- SD) after a single intravenous dose of 5 mcg of doxercalciferol. The mean elimination half-life of 1α,25-(OH)2D2 after an oral dose is approximately 32 to 37 hours with a range of up to 96 hours. The mean elimination half-life in patients with end stage renal disease (ESRD) and in healthy volunteers appears to be similar following an oral dose. Hemodialysis causes a temporary increase in 1α,25-(OH)2D2 mean concentrations presumably due to volume contraction. 1α,25-(OH)2D2 is not removed from blood during hemodialysis.

Clinical Studies

The safety and effectiveness of doxercalciferol injection were evaluated in two open-label, single-arm, multi-centered clinical studies (Study C and Study D) in a total of 70 patients with chronic kidney disease on hemodialysis (Stage 5 CKD). Patients in Study C were an average age of 54 years (range: 23 to 73), were 50% male, and were 61% African-American, 25% Caucasian, and 14% Hispanic, and had been on hemodialysis for an average of 65 months. Patients in Study D were an average age of 51 years (range: 28 to 76), were 48% male, and 100% African-American and had been on hemodialysis for an average of 61 months. This group of 70 of the 138 patients who had been treated with doxercalciferol capsules in prior clinical studies (Study A and Study B) received doxercalciferol injection in an open-label fashion for 12 weeks following an 8-week washout (control) period. Dosing of doxercalciferol injection was initiated at the rate of 4 mcg administered at the end of each dialysis session (3 times weekly) for a total of 12 mcg per week. The dosage of doxercalciferol was adjusted in an attempt to achieve iPTH levels within a targeted range of 150 to 300 pg/mL. The dosage was increased by 2 mcg per dialysis session after 8 weeks of treatment if the iPTH levels remained above 300 pg/mL and were greater than 50% of baseline levels. The maximum dosage was limited to 18 mcg per week. If at any time during the trial iPTH fell below 150 pg/mL, doxercalciferol injection was immediately suspended and restarted at a lower dosage the following week.

Results

Fifty-two of the 70 patients who were treated with doxercalciferol injection achieved iPTH levels ≤ 300 pg/mL. Forty-one of these patients exhibited plasma iPTH levels ≤ 300 pg/mL on at least three occasions. Thirty-six patients had plasma iPTH levels < 150 pg/mL on at least one occasion during study participation.

Mean weekly doses in Study C ranged from 8.9 mcg to 12.5 mcg. In Study D, the mean weekly doses ranged from 9.1 mcg to 11.6 mcg.

Decreases in plasma iPTH from baseline values were calculated using as baseline the average of the last three values obtained during the 8-week washout period and are displayed in the table below. Plasma iPTH levels were measured weekly during the 12-week study.

Table 1: iPTH Summary Data for Patients Receiving Doxercalciferol Injection
iPTH Level | Study C (n = 28) | Study D (n = 42) | Combined Protocols (n = 70)
Baseline (Mean of Weeks -2, -1 and 0)
Mean (SE) | 698 (60) | 762 (65) | 736 (46)
Median | 562 | 648 | 634
On-treatment (Week 12 [Values were carried forward for the two patients on study for 10 weeks])
Mean (SE) | 406 (63) | 426 (60) | 418 (43)
Median | 311 | 292 | 292
Change from Baseline [Treatment iPTH minus baseline iPTH]
Mean (SE) | -292 (55) | -336 (41) | -318 (33)
Median | -274 | -315 | -304
P-value [Wilcoxon one-sample test] | 0.004 | 0.001 | < 0.001

In both studies, iPTH levels increased progressively and significantly in 62.9% of patients during the 8-week washout (control) period during which no vitamin D derivatives were administered. In contrast, doxercalciferol injection treatment resulted in a clinically significant reduction (at least 30%) from baseline in mean iPTH levels during the 12-week open-label treatment period in more than 92% of the 70 treated patients.

Table 2 shows the numbers of patients who achieved iPTH levels below 300 pg/mL on one, two, or three or more non-consecutive occasions during the 12-week treatment period. Thirty-seven of 70 patients (53%) had plasma iPTH levels within the targeted range (150 to 300 pg/mL) during Weeks 10 to 12.

Table 2: Number of Times iPTH ≤ 300 pg/mL
 | 1 | 2 | ≥3
Study C | 3/28 | 0/28 | 16/28
Study D | 4/42 | 4/42 | 25/42

INDICATIONS AND USAGE

Doxercalciferol injection is indicated for the treatment of secondary hyperparathyroidism in patients with chronic kidney disease on dialysis.

CONTRAINDICATIONS

Doxercalciferol injection should not be given to patients with a tendency towards hypercalcemia or current evidence of vitamin D toxicity.

Doxercalciferol injection is contraindicated in patients with previous hypersensitivity to doxercalciferol or any of its ingredients (see WARNINGS and ADVERSE REACTIONS).

WARNINGS

Overdosage of any form of vitamin D, including doxercalciferol injection is dangerous (see OVERDOSAGE). Progressive hypercalcemia due to overdosage of vitamin D and its metabolites may be so severe as to require emergency attention. Acute hypercalcemia may exacerbate tendencies for cardiac arrhythmias and seizures and may potentiate the action of digitalis drugs. Chronic hypercalcemia can lead to generalized vascular calcification and other soft-tissue calcification. The serum calcium times serum phosphorus (Ca X P) product should be maintained at < 55 mg^2/dL^2 in patients with chronic kidney disease. Radiographic evaluation of suspect anatomical regions may be useful in the early detection of this condition.

Since doxercalciferol is a precursor for 1α,25-(OH)2D2, a potent metabolite of vitamin D2, pharmacologic doses of vitamin D and its derivatives should be withheld during doxercalciferol injection treatment to avoid possible additive effects and hypercalcemia.

Oral calcium-based or other non-aluminum-containing phosphate binders and a low phosphate diet should be used to control serum phosphorus levels in patients undergoing dialysis. Uncontrolled serum phosphorus exacerbates secondary hyperparathyroidism and can lessen the effectiveness of doxercalciferol injection in reducing blood PTH levels. If hypercalcemia occurs after initiating doxercalciferol injection therapy, the dose of doxercalciferol injection and/or calcium-containing phosphate binders should be decreased. If hyperphosphatemia occurs after initiating doxercalciferol injection, the dose of doxercalciferol injection should be decreased and/or the dose of phosphate binders increased. (See dosing recommendations for doxercalciferol injection under DOSAGE AND ADMINISTRATION.)

Magnesium-containing antacids and doxercalciferol injection should not be used concomitantly in patients on chronic renal dialysis because such use may lead to the development of hypermagnesemia.

Serious hypersensitivity reactions, including fatal outcome, have been reported post marketing in patients on hemodialysis following administration of doxercalciferol injection. Hypersensitivity reactions include anaphylaxis with symptoms of angioedema (involving face, lips, tongue and airways), hypotension, unresponsiveness, chest discomfort, shortness of breath, and cardiopulmonary arrest. These reactions may occur separately or together.

Monitor patients receiving doxercalciferol injection upon initiation of treatment for hypersensitivity reactions. Should a hypersensitivity reaction occur, discontinue doxercalciferol, monitor and treat if indicated (see CONTRAINDICATIONS).

PRECAUTIONS

General

The principal adverse effects of treatment with doxercalciferol injection are hypercalcemia, hyperphosphatemia, and oversuppression of PTH (iPTH less than 150 pg/mL). Prolonged hypercalcemia can lead to calcification of soft tissues, including the heart and arteries, and hyperphosphatemia can exacerbate hyperparathyroidism. Oversuppression of PTH may lead to adynamic bone syndrome. All of these potential adverse effects should be managed by regular patient monitoring and appropriate dosage adjustments. During treatment with doxercalciferol injection, patients usually require dose titration, as well as adjustment in co-therapy (i.e., dietary phosphate binders) in order to maximize PTH suppression while maintaining serum calcium and phosphorus levels within prescribed ranges.

In two open-label, single-arm, multi-centered studies, the incidence of hypercalcemia and hyperphosphatemia increased during therapy with doxercalciferol injection (see ADVERSE REACTIONS). The observed increases during doxercalciferol injection treatment underscore the importance of regular safety monitoring of serum calcium and phosphorus levels throughout treatment. Patients with higher pre-treatment serum levels of calcium (> 10.5 mg/dL) or phosphorus (> 6.9 mg/dL) were more likely to experience hypercalcemia or hyperphosphatemia. Therefore, doxercalciferol injection should not be given to patients with a recent history of hypercalcemia or hyperphosphatemia, or evidence of vitamin D toxicity.

Table 3: Incidence Rates of Hypercalcemia and Hyperphosphatemia in Two Phase 3 Studies with Doxercalciferol Injection
Study | Hypercalcemia (per 100 patient weeks) |  | Hyperphosphatemia (per 100 patient weeks)
 | Washout (Off Treatment) | Open-Label (Treatment) | Washout (Off Treatment) | Open-Label (Treatment)
Study C | 0.9 | 0.9 | 0.9 | 2.4
Study D | 0.3 | 1 | 1.2 | 3.7

Information for the Patient

The patient, spouse, or guardian should be informed about adherence to instructions about diet, calcium supplementation, and avoidance of the use of nonprescription drugs without prior approval from the patient’s physician. Patients should also be carefully informed about the symptoms of hypercalcemia (see ADVERSE REACTIONS).

Laboratory Tests

Serum levels of iPTH, calcium, and phosphorus should be determined prior to initiation of doxercalciferol injection treatment. During the early phase of treatment (i.e., first 12 weeks), serum iPTH, calcium, and phosphorus levels should be determined weekly. For dialysis patients in general, serum or plasma iPTH and serum calcium, phosphorus, and alkaline phosphatase should be determined periodically.

Drug Interactions

Specific drug interaction studies have not been conducted. Magnesium-containing antacids and doxercalciferol should not be used concomitantly because such use may lead to the development of hypermagnesemia (see WARNINGS). Although not examined specifically, enzyme inducers (such as glutethimide and phenobarbital) may affect the 25-hydroxylation of doxercalciferol and may necessitate dosage adjustments. Cytochrome P450 inhibitors (such as ketoconazole and erythromycin) may inhibit the 25-hydroxylation of doxercalciferol. Hence, formation of the active doxercalciferol moiety may be hindered.

Carcinogenesis, Mutagenesis, Impairment of Fertility

Long-term studies in animals to evaluate the carcinogenic potential of doxercalciferol have not been conducted. No evidence of genetic toxicity was observed in an in vitro bacterial mutagenicity assay (Ames test) or a mouse lymphoma gene mutation assay. Doxercalciferol caused structural chromatid and chromosome aberrations in an in vitro human lymphocyte clastogenicity assay with metabolic activation. However, doxercalciferol was negative in an in vivo mouse micronucleus clastogenicity assay. Doxercalciferol had no effect on male or female fertility in rats at oral doses up to 2.5 mcg/kg/day (approximately 3 times the maximum recommended human oral dose of 60 mcg/wk based on mcg/m^2 body surface area).

Use in Pregnancy

Pregnancy Category B

Reproduction studies in rats and rabbits, at doses up to 20 mcg/kg/day and 0.1 mcg/kg/day (approximately 25 times and less than the maximum recommended human oral dose of 60 mcg/week based on mcg/m^2 body surface area, respectively) have revealed no teratogenic or fetotoxic effects due to doxercalciferol. There are, however, no adequate and well controlled studies in pregnant women. Because animal reproduction studies are not always predictive of human response, this drug should be used during pregnancy only if clearly needed.

Nursing Mothers

It is not known whether doxercalciferol is excreted in human milk. Because other vitamin D derivatives are excreted in human milk and because of the potential for serious adverse reactions in nursing infants from doxercalciferol, a decision should be made whether to discontinue nursing or to discontinue the drug, taking into account the importance of the drug to the mother.

Pediatric Use

Safety and efficacy of doxercalciferol injection in pediatric patients have not been established.

Geriatric Use

Of the 70 patients treated with doxercalciferol injection in the two Phase 3 clinical studies, 12 patients were 65 years or over. In these studies, no overall differences in efficacy or safety were observed between patients 65 years or older and younger patients.

Hepatic Insufficiency

Studies examining the influence of hepatic insufficiency on the metabolism of doxercalciferol were inconclusive. Since patients with hepatic insufficiency may not metabolize doxercalciferol appropriately, the drug should be used with caution in patients with impaired hepatic function. More frequent monitoring of iPTH, calcium, and phosphorus levels should be done in such individuals.

ADVERSE REACTIONS

Doxercalciferol injection has been evaluated for safety in 70 patients with chronic renal disease on hemodialysis (who had been previously treated with oral doxercalciferol) from two 12-week, open-label, single-arm, multi-centered studies. (Dosage titrated to achieve target plasma iPTH levels, see CLINICAL PHARMACOLOGY, Clinical Studies.)

Because there was no placebo group included in the studies of doxercalciferol injection, Table 4 provides the adverse event incidence rates from placebo-controlled studies of oral doxercalciferol.

Table 4: Adverse Events Reported by ≥ 2% of Doxercalciferol Injection Treated Patients and More Frequently than Placebo During the Double-Blind Phase of Two Clinical Studies
Adverse Event | Doxercalciferol Injection (n = 61) % | Placebo (n = 61) %
Body as a Whole
Abscess | 3.3 | 0.0
Headache | 27.9 | 18.0
Malaise | 27.9 | 19.7
Cardiovascular System
Bradycardia | 6.6 | 4.9
Digestive System
Anorexia | 4.9 | 3.3
Constipation | 3.3 | 3.3
Dyspepsia | 4.9 | 1.6
Nausea/Vomiting | 21.3 | 19.7
Musculoskeletal System
Arthralgia | 4.9 | 0.0
Metabolic and Nutritional
Edema | 34.4 | 21.3
Weight increase | 4.9 | 0.0
Nervous System
Dizziness | 11.5 | 9.8
Sleep Disorder | 3.3 | 0.0
Respiratory System
Dyspnea | 11.5 | 6.6
Skin
Pruritus | 8.2 | 6.6
A patient who reported the same medical term more than once was counted only once for that medical term.

Potential adverse effects of doxercalciferol injection are, in general, similar to those encountered with excessive vitamin D intake. The early and late signs and symptoms of vitamin D intoxication associated with hypercalcemia include:

Early
Weakness, headache, somnolence, nausea, vomiting, dry mouth, constipation, muscle pain, bone pain, metallic taste, and anorexia.

Late
Polyuria, polydipsia, anorexia, weight loss, nocturia, conjunctivitis (calcific), pancreatitis, photophobia, rhinorrhea, pruritus, hyperthermia, decreased libido, elevated blood urea nitrogen (BUN), albuminuria, hypercholesterolemia, elevated serum aspartate transaminase (AST) and alanine transaminase (ALT), ectopic calcification, hypertension, cardiac arrhythmias, sensory disturbances, dehydration, apathy, arrested growth, urinary tract infections, and, rarely, overt psychosis.

Postmarketing Experience

Because these reactions are reported voluntarily from a population of uncertain size, it is not always possible to estimate their frequency or to establish a causal relationship to drug exposure.

Hypersensitivity reactions, including fatal outcome, have been reported in patients on hemodialysis following administration of doxercalciferol injection. Hypersensitivity reactions include anaphylaxis with symptoms of angioedema (involving face, lips, tongue and airways), hypotension, unresponsiveness, chest discomfort, shortness of breath, cardiopulmonary arrest, pruritus and skin burning sensation (see WARNINGS). These reactions may occur separately or together.

OVERDOSAGE

Administration of doxercalciferol injection to patients in excess doses can cause hypercalcemia, hypercalciuria, hyperphosphatemia, and over-suppression of PTH secretion leading in certain cases to adynamic bone disease. High intake of calcium and phosphate concomitant with doxercalciferol injection may lead to similar abnormalities. High levels of calcium in the dialysate bath may contribute to hypercalcemia.

Treatment of Hypercalcemia and Overdosage

General treatment of hypercalcemia (greater than 1 mg/dL above the upper limit of the normal range) consists of immediate suspension of doxercalciferol injection therapy, institution of a low calcium diet, and withdrawal of calcium supplements. Serum calcium levels should be determined at least weekly until normocalcemia ensues. Hypercalcemia usually resolves in 2 to 7 days. When serum calcium levels have returned to within normal limits, doxercalciferol injection therapy may be reinstituted at a dose that is at least 1 mcg lower than prior therapy. Serum calcium levels should be obtained weekly after all dosage changes and during subsequent dosage titration. Persistent or markedly elevated serum calcium levels may be corrected by dialysis against a reduced calcium or calcium-free dialysate.

Treatment of Accidental Overdosage of Doxercalciferol Injection

The treatment of acute accidental overdosage of doxercalciferol injection should consist of general supportive measures. Serial serum electrolyte determinations (especially calcium), rate of urinary calcium excretion, and assessment of electrocardiographic abnormalities due to hypercalcemia should be obtained. Such monitoring is critical in patients receiving digitalis. Discontinuation of supplemental calcium and institution of a low calcium diet are also indicated in accidental overdosage. If persistent and markedly elevated serum calcium levels occur, treatment with standard medical care should be followed, as needed. Based on similarities between doxercalciferol and its active metabolite, 1α,25-(OH)2D2, it is expected that doxercalciferol is not removed from the blood by dialysis.

DOSAGE AND ADMINISTRATION

Adult Administration:

For intravenous use only. The optimal dose of doxercalciferol injection must be carefully determined for each patient.

The recommended initial dose of doxercalciferol injection is 4 mcg administered intravenously as a bolus dose 3 times weekly at the end of dialysis (approximately every other day). The initial dose should be adjusted, as needed, in order to lower blood iPTH into the range of 150 to 300 pg/mL. The dose may be increased at 8-week intervals by 1 mcg to 2 mcg if iPTH is not lowered by 50% and fails to reach the target range. Dosages higher than 18 mcg weekly have not been studied. Drug administration should be suspended if iPTH falls below 100 pg/mL and restarted one week later at a dose that is at least 1 mcg lower than the last administered dose. During titration, iPTH, serum calcium, and serum phosphorus levels should be obtained weekly. If hypercalcemia, hyperphosphatemia, or a serum calcium times phosphorus product greater than 55 mg^2/dL^2 is noted, the dose of doxercalciferol injection should be decreased or suspended and/or the dose of phosphate binders should be appropriately adjusted. If suspended, the drug should be restarted at a dose that is 1 mcg lower.

Dosing must be individualized and based on iPTH levels with monitoring of serum calcium and serum phosphorus levels. Table 5 presents a suggested approach in dose titration:

Table 5: Initial Dosing
iPTH Level | Doxercalciferol Injection Dose
> 400 pg/mL | 4 mcg 3 times per week at the end of dialysis, or approximately every other day
 | Dose Titration
iPTH Level | Doxercalciferol Injection Dose
Decreased by < 50% and above 300 pg/mL | Increase by 1 mcg to 2 mcg at 8-week intervals as necessary
Decreased by > 50% and above 300 pg/mL | Maintain
150 to 300 pg/mL | Maintain
< 100 pg/mL | Suspend for one week, then resume at a dose that is at least 1 mcg lower

HOW SUPPLIED

Doxercalciferol Injection is available in the following package:

4 mcg/2 mL (2 mcg/mL), 2 mL pre-scored amber ampuls packaged in 25s (NDC 0641-6154-25)

Store at 25°C (77°F), excursions permitted to 15 to 30°C (59 to 86°F) [See USP Controlled Room Temperature].

Protect from light.

To report SUSPECTED ADVERSE REACTIONS, contact West-Ward Pharmaceuticals Corp. at 1-877-845-0689, or the FDA at 1-800-FDA-1088 or www.fda.gov/medwatch.

For Product Inquiry call 1-877-845-0689.

Manufactured by:
HIKMA FARMACÊUTICA (PORTUGAL), S.A.
Estrada do Rio da Mό, 8, 8A e 8B – Fervença – 2705-906 Terrugem SNT, PORTUGAL

Distributed by:
WEST-WARD
A Hikma Company
Eatontown, NJ 07724 USA

PIN349-WES/2

Revised July 2016

PRINCIPAL DISPLAY PANEL - Container

NDC 0641-6154-01
2 mL Ampul
Doxercalciferol
Injection
Rx only
4 mcg/2 mL (2 mcg/mL)
For Intravenous Use Only
Protect From Light
Discard Unused Portion

PRINCIPAL DISPLAY PANEL - Carton

NDC 0641-6154-25 Rx only
Doxercalciferol
Injection
4 mcg/2 mL
(2 mg/mL)
For Intravenous Use Only
Protect From Light
Discard Unused Portion
25 x 2 mL Ampuls

CONTENTS
Active Ingredient: Doxercalciferol, 0.0002%
Inactive ingredients: Polysorbate 20, 0.4%;
Sodium Chloride, 0.15%; Sodium Ascorbate, 1.0%;
Sodium Phosphate, Dibasic, Anhydrous, 0.76%;
Sodium Dihydrogen Phosphate, Dihydrate, 0.234%;
Edetate, Disodium, Dihydrate, 0.11%;
Water for Injection, 97.35%

Usual Dosage: See accompanying prescribing
information.
Store at 20° to 25°C (68° to 77°F)
[See USP Controlled Room Temperature].
PROTECT FROM LIGHT: Keep covered in carton
until time of use.